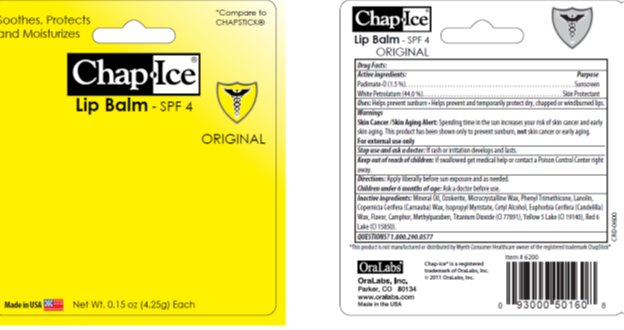 DRUG LABEL: ChapIce Original SPF 4 Lip Balm
NDC: 63645-130 | Form: STICK
Manufacturer: OraLabs
Category: otc | Type: HUMAN OTC DRUG LABEL
Date: 20220127

ACTIVE INGREDIENTS: PETROLATUM 44.0 mg/1 g; PADIMATE O 1.5 mg/1 g
INACTIVE INGREDIENTS: MICROCRYSTALLINE WAX 3.00 mg/1 g; LANOLIN 1 mg/1 g; CERESIN 17.30 mg/1 g; CARNAUBA WAX 1 mg/1 g; ISOPROPYL MYRISTATE 2.23 mg/1 g; LIGHT MINERAL OIL 27.50 mg/1 g

Drug Facts

Active ingredient

Padimate O, Petrolatum

Purpose

Sunscreen, Skin Protectant

Keep Out of Reach of Children

If swallowed get medical help or contact a Poison Control Center right away.

Uses

Helps prevent sunburn. Helps prevent and temporarily protects dry, chapped or windburned lips.

Warnings

Skin Cancer/Skin Aging Alert: Spending time in the sun increases your risk of skin cancer and early skin aging. This product has been shown only to prevent sunburn, not skin cancer or early aging.

For external use only

Stop use and ask a doctor: If rash or irritation develops and lasts.

Directions

Apply liberally before sun exposure and as needed.

Children under 6 months of age: Ask a doctor before use.

Inactive Ingredients

Mineral Oil, Ozokerite, Microcrystalline Wax, Phenyl Trimethicone, Lanolin, Copercicia (Carnauba) Wax, Isopropyl Myristate, Cetyl Alcohol, Euphorbia Cerifera (Candelilla) Wax, Flavor, Camphor, Methylparaben, Titanium Dioxide (CI 77891), Yellow 5 Lake (CI 19140), Red 6 Lake (CI 15850).